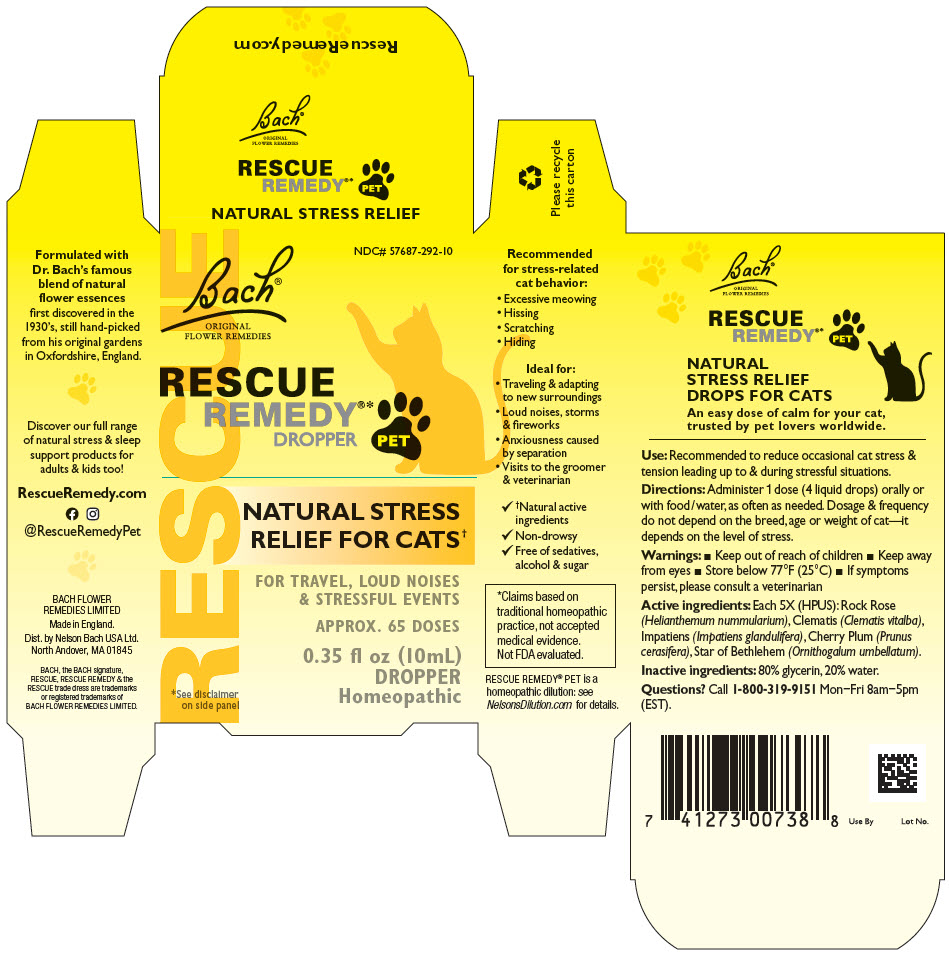 DRUG LABEL: Rescue Remedy Pet
NDC: 57687-292 | Form: SOLUTION
Manufacturer: Nelson Bach USA Limited
Category: homeopathic | Type: OTC ANIMAL DRUG LABEL
Date: 20210512

ACTIVE INGREDIENTS: HELIANTHEMUM NUMMULARIUM WHOLE 5 [hp_X]/0.095 mL; CLEMATIS VITALBA TOP 5 [hp_X]/0.095 mL; IMPATIENS GLANDULIFERA WHOLE 5 [hp_X]/0.095 mL; PRUNUS CERASIFERA WHOLE 5 [hp_X]/0.095 mL; ORNITHOGALUM UMBELLATUM WHOLE 5 [hp_X]/0.095 mL
INACTIVE INGREDIENTS: Glycerin; Water

Rescue Remedy® Pet

Bach®
ORIGINAL
FLOWER REMEDIES

NATURAL STRESS RELIEF DROPS FOR CATS

An easy dose of calm for your cat, trusted by pet lovers worldwide.

VETERINARY INDICATIONS

Use: Recommended to reduce occasional cat stress & tension leading up to & during stressful situations.

DOSAGE AND ADMINISTRATION

Directions: Administer 1 dose (4 liquid drops) orally or with food/water, as often as needed. Dosage & frequency do not depend on the breed, age or weight of cat—it depends on the level of stress.

Warnings:

- Keep out of reach of children
- Keep away from eyes
- Store below 77°F (25°C)
- If symptoms persist, please consult a veterinarian

ACTIVE INGREDIENT

Active ingredients: Each 5X (HPUS): Rock Rose (Helianthemum nummularium), Clematis (Clematis vitalba), Impatiens (Impatiens glandulifera), Cherry Plum (Prunus cerasifera), Star of Bethlehem (Ornithogalum umbellatum).

Inactive ingredients: 80% glycerin, 20% water.

QUESTIONS

Questions? Call 1-800-319-9151 Mon−Fri 8am−5pm (EST).

Recommended for stress-related cat behavior:

- Excessive meowing
- Hissing
- Scratching
- Hiding

Ideal for:

- Traveling & adapting to new surroundings
- Loud noises, storms & fireworks
- Anxiousness caused by separation
- Visits to the groomer & veterinarian

✓ †Natural active ingredients
✓ Non-drowsy
✓ Free of sedatives, alcohol & sugar

*Claims based on traditional homeopathic practice, not accepted medical evidence. Not FDA evaluated.

RESCUE REMEDY® PET is a homeopathic dilution: see NelsonsDilution.com for details.

Formulated with Dr. Bach's famous blend of natural flower essences first discovered in the 1930's, still hand-picked from his original gardens in Oxfordshire, England.

Discover our full range of natural stress & sleep support products for adults & kids too!

RescueRemedy.com

@RescueRemedyPet

BACH FLOWER
REMEDIES LIMITED

Made in England.
Dist. by Nelson Bach USA Ltd.
North Andover, MA 01845

BACH, the BACH signature, RESCUE, RESCUE REMEDY & the RESCUE trade dress are trademarks or registered trademarks of BACH FLOWER REMEDIES LIMITED.

PRINCIPAL DISPLAY PANEL - 10 mL Bottle Carton

RESCUE

NDC# 57687-292-10

Bach®
ORIGINAL
FLOWER REMEDIES

RESCUE
REMEDY®*
DROPPER
PET

NATURAL STRESS
RELIEF FOR CATS†

FOR TRAVEL, LOUD NOISES
& STRESSFUL EVENTS

APPROX. 65 DOSES

0.35 fl oz (10mL)
DROPPER
Homeopathic

*See disclaimer
on side panel